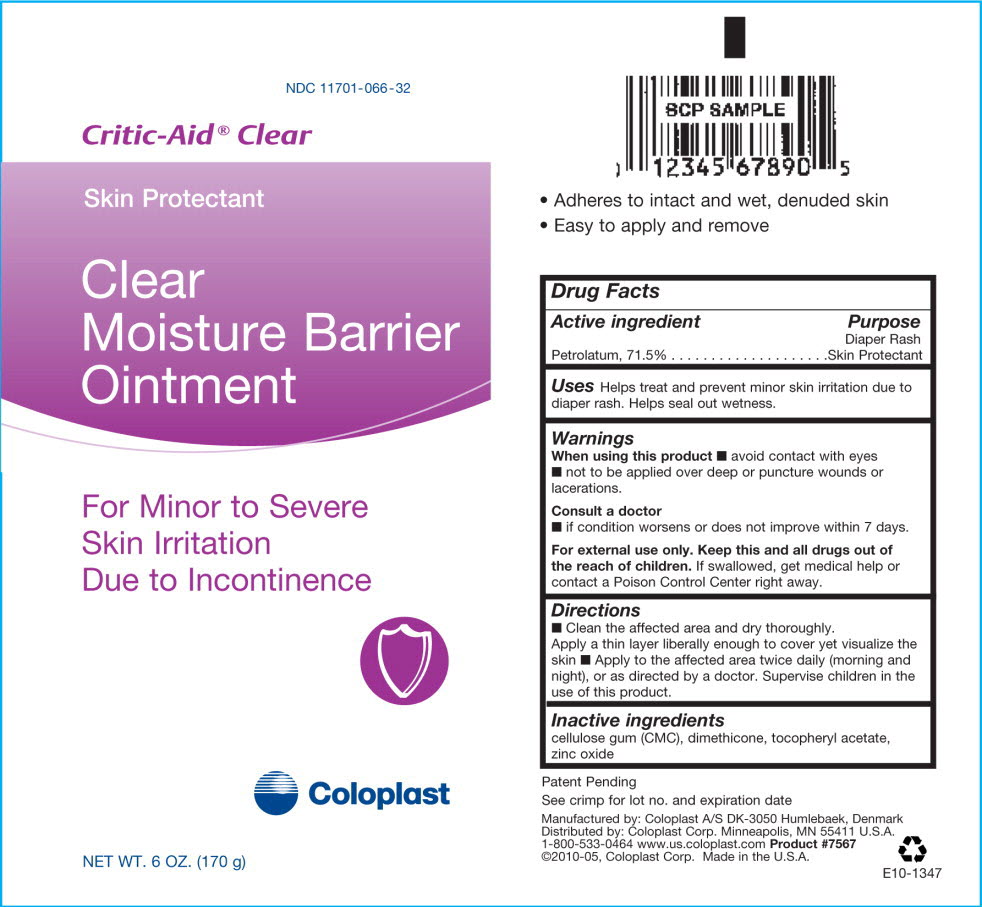 DRUG LABEL: Critic Aid Clear
NDC: 11701-066 | Form: OINTMENT
Manufacturer: Coloplast Manufacturing US, LLC
Category: otc | Type: HUMAN OTC DRUG LABEL
Date: 20231221

ACTIVE INGREDIENTS: PETROLATUM 710 mg/1 g
INACTIVE INGREDIENTS: .ALPHA.-TOCOPHEROL ACETATE, D-; DIMETHICONE; ZINC OXIDE; CROSCARMELLOSE SODIUM

Critic-Aid® Clear
Skin Protectant
Clear Moisture Barrier Ointment

For Minor To Severe
Skin Irritation
Due To Incontinence

- Adheres to denuded skin
- Easy to apply and remove
- Eliminates moisture

Drug Facts

Active ingredient

Petrolatum, 71.5%

Purpose

Diaper Rash Skin Protectant

INDICATIONS AND USAGE

Uses Helps treat and prevent minor skin irritation due to diaper rash. Helps seal out wetness.

Warnings

When using this product

- avoid contact with eyes
- not to be applied over deep or puncture wounds or lacerations.

Consult a doctor

- if condition worsens or does not improve within 7 days.

KEEP OUT OF REACH OF CHILDREN

For external use only. Keep this and all drugs out of the reach of children. If swallowed, get medical help or contact a Poison Control Center right away.

Directions

- change wet and soiled diapers promptly, cleanse the diaper area, and allow to dry
- apply liberally as often as necessary, with each diaper change, especially at bedtime or any time when exposure to wet diapers may be prolonged.

Inactive ingredients

cellulose gum, dimethicone, tocopheryl acetate, zinc oxide

Patent Pending

See crimp for lot no. and expiration date

Manufactured by: Coloplast A/S DK-3050 Humlebaek, Denmark
Distributed by: Coloplast Corp. Minneapolis, MN 55411 U.S.A.
1-800-533-0464 www.us.coloplast.com Product #7567
©2007, Coloplast Corp. Made in the U.S.A.

E10-1347

PACKAGE LABEL

PRINCIPAL DISPLAY PANEL - NET WT. 6 OZ. (170 g)

NDC 11701-066-32

Critic-Aid® Clear

Skin Protectant

Clear Moisture Barrier Ointment

For Minor To Severe

Skin Irritation

Due To Incontinence

Coloplast

NET WT. 6 OZ. (170 g)